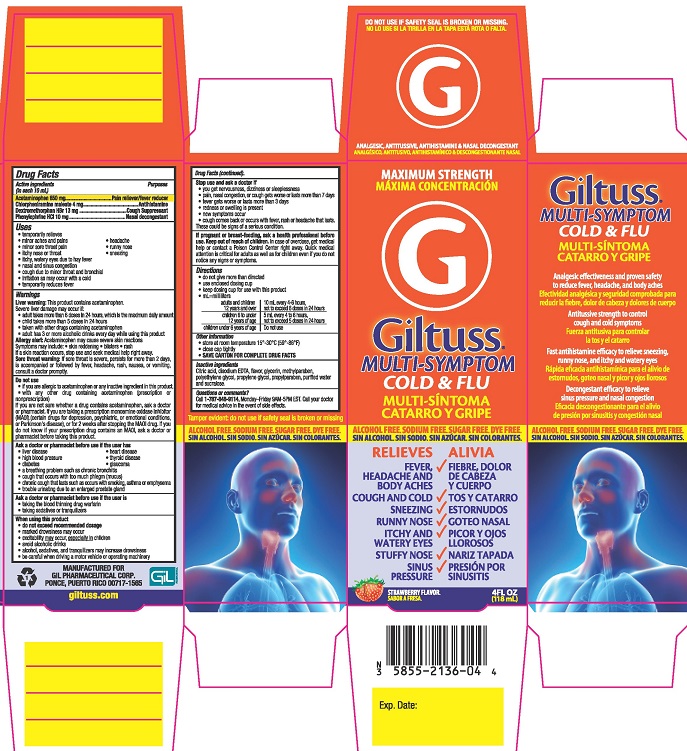 DRUG LABEL: Giltuss MultiSymptom Cold and Flu
NDC: 58552-136 | Form: SOLUTION
Manufacturer: Giltuss Pharmaceutical Corp
Category: otc | Type: HUMAN OTC DRUG LABEL
Date: 20251009

ACTIVE INGREDIENTS: CHLORPHENIRAMINE MALEATE 4 mg/10 mL; PHENYLEPHRINE HYDROCHLORIDE 10 mg/10 mL; DEXTROMETHORPHAN HYDROBROMIDE 13 mg/10 mL; ACETAMINOPHEN 650 mg/10 mL
INACTIVE INGREDIENTS: POLYETHYLENE GLYCOL, UNSPECIFIED; ANHYDROUS CITRIC ACID; PROPYLPARABEN; GLYCERIN; PROPYLENE GLYCOL; WATER; SUCRALOSE; EDETATE DISODIUM; METHYLPARABEN

Giltuss Multi-Symptom Cold & Flu

Drug Facts

Active ingredients (in each 10 mL)

Acetaminophen 650 mg

Chlorpheniramine maleate 4 mg

Dextromethorphan hydrobromide 13 mg

Phenylephrine hydrochloride 10 mg

Purposes

Pain reliever/fever reducer

Antihistamine

Cough Suppressant

Nasal decongestant

Uses

- temporarily relieves:
- minor aches and pains
- headache
- minor sore throat pain
- runny nose
- itchy nose or throat
- sneezing
- itchy watery eyes due to hay fever
- nasal and sinus congestion
- cough due to minor throat and bronchial irritation as may occur with a cold
- temporarily reduces fever

Warnings

Liver warning:This product contains acetaminophen. Severe liver damage may occur if:

- adult takes more than 6 doses in 24 hours, which is the maximum daily amount
- child takes more than 5 doses in 24 hours
- taken with other drugs containing acetaminophen
- adult has 3 or more alcoholic drinks every day while using this product

Allergy alert:Acetaminophen may cause severe skin reactions. Symptoms may include:

- skin reddening
- blisters
- rash
- hives
- facial swelling
- asthma (wheezing)
- shock

If a skin reaction occurs, stop use and seek medical help right away.

Sore throat warning:If sore throat is severe, persists for more than 2 days, is accompanied or followed by fever, headache, rash, nausea, or vomiting, consult a doctor promptly.

Do not use

- if you are allergic to acetaminophen or any inactive ingredient in this product
- with any other drug containing acetaminophen (prescription or nonprescription). If you are not sure whether a drug contains acetaminophen, ask a doctor or pharmacist.
- if you are now taking a prescription monoamine oxidase inhibitor (MAOI) (certain drugs for depression, psychiatric, or emotional conditions, or Parkinson's disease), or for 2 weeks after stopping the MAOI drug. If you do not know if your prescription drug contains an MAOI, ask a doctor or pharmacist before taking this product.

Ask a doctor or pharmacist before use if the user has

- liver disease
- heart disease
- high blood pressure
- thyroid disease
- diabetes
- glaucoma
- a breathing problem such as chronic bronchitis
- cough that occurs with too much phlegm (mucus)
- chronic cough that lasts such as occurs with smoking, asthma, or emphysema
- trouble urinating due to enlargement of the prostate gland

Ask a doctor or pharmacist before use if the user is

- taking the blood thinning drug warfarin
- taking sedatives or tranquilizers

When using this product

- do not exceed recommended dosage
- marked drowsiness may occur
- excitability may occur, especially in children
- avoid alcoholic drinks
- alcohol, sedatives, and tranquilizers may increase drowsiness
- be careful when driving a motor vehicle or operating machinery

Stop use and ask a doctor if

- you get nervousness, dizzyness or sleeplessness
- pain, nasal congestion, or cough gets worse or lasts more than 7 days
- fever gets worse or lasts more than 3 days
- redness or swelling is present
- new symptoms occur
- cough comes back or occurs with fever, rash or headache that lasts.

These could be signs of a serious condition.

PREGNANCY OR BREAST FEEDING

If pregnant or breast-feeding, ask a health professional before use.

Keep out of reach of children. In case of overdose, get medical help or contact a Poison Control Center right away. Quick medical attention is critical for adults as well as for children even if you do not notice any signs or symptoms.

Directions

- do not give more than directed
- use enclosed dosing cup
- keep dosing cup for use with this product
- mL = milliliter

adults and children 12 years and over | 10 mL every 4-6 hours, not to exceed 6 doses in 2 hours
children 6 to under 12 years of age | 5 mL every 4-6 hours, not to exceed 5 doses in 24 hours
children under 6 years of age | Do not use

Other information

- store at room temperature 15° - 30°C (59° - 86°F)
- close cap tightly
- SAVE CARTON FOR COMPLETE DRUG FACTS

INACTIVE INGREDIENT

Inactive ingredientscitric acid, disodium EDTA, flavor, glycerin, methylparaben, polyethylene glycol, propylene glycol, propylparaben, purified water and sucralose

Questions or comments?

Call 1-787-848-9114,Monday-Friday 9AM - 5PM EST. Call your doctor for medical advice in the event of side effects.

Tamper evident: do not use if safety seal is broken or missing

MANUFACTURED FOR

GIL PHARMACEUTICAL CORP.

PONCE, PUERTO RICO 00717-1565

PACKAGE LABEL

MAXIMUM STRENGTH

Giltuss® MULTI-SYMPTOM

COLD & FLU

ANALGESIC, ANTITUSSIVE, ANTIHISTAMINE & NASAL DECONGESTANT

ALCOHOL FREE. SODIUM FREE. SUGAR FREE. DYE FREE

RELIEVES

- FEVER, HEADACHE AND BODY ACHES
- COUGH AND COLD
- SNEEZING
- RUNNY NOSE
- ITCHY AND WATERY EYES
- STUFFY NOSE
- SINUS PRESSURE

STRAWBERRY FLAVOR

4FL OZ (118 mL)